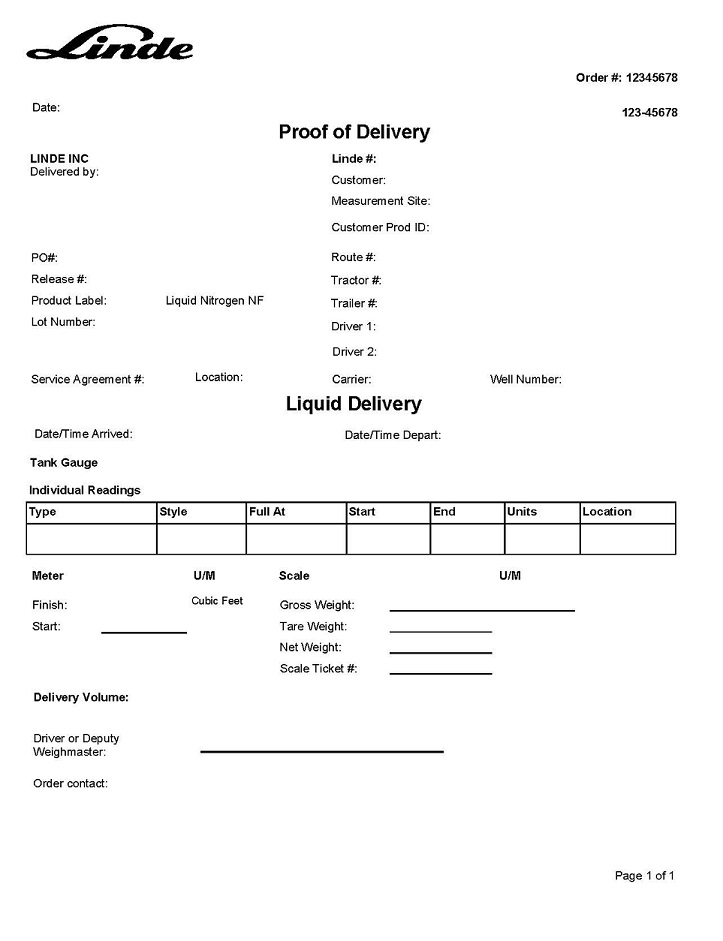 DRUG LABEL: Nitrogen
NDC: 59578-499 | Form: GAS
Manufacturer: Linde Inc.
Category: prescription | Type: HUMAN PRESCRIPTION DRUG LABEL
Date: 20251230

ACTIVE INGREDIENTS: NITROGEN 990 mL/1 L

Liquid Nitrogen NF